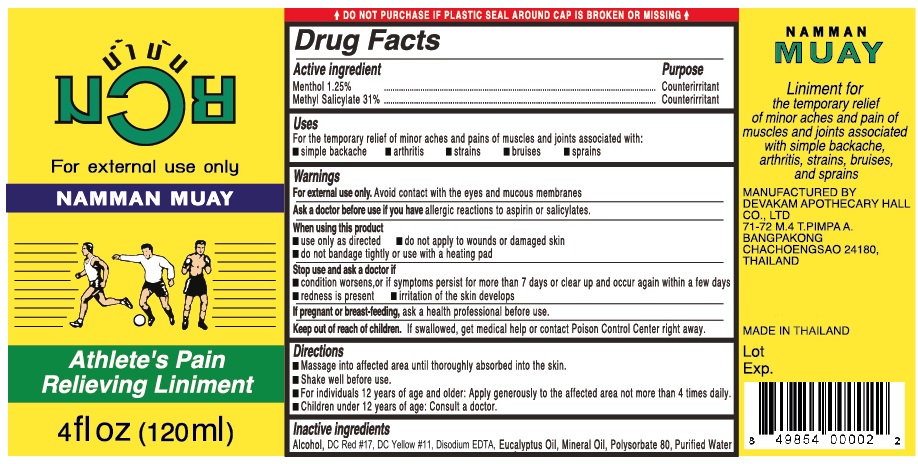 DRUG LABEL: Namman Muay Pain Relieving
NDC: 43599-000 | Form: LINIMENT
Manufacturer: Devakam Apothecary Hall, Co, Ltd.
Category: otc | Type: HUMAN OTC DRUG LABEL
Date: 20201002

ACTIVE INGREDIENTS: MENTHOL 12.5 mg/1 mL; METHYL SALICYLATE 310 mg/1 mL
INACTIVE INGREDIENTS: ALCOHOL; D&C RED NO. 17; D&C YELLOW NO. 11; EDETATE DISODIUM ANHYDROUS; EUCALYPTUS OIL; MINERAL OIL; POLYSORBATE 80; WATER

Namman Muay Pain Relieving Liniment

Active ingredient

Menthol 1.25%

Methyl Salicylate 31%

Purpose

Counterirritant

Uses

For the temporary relief of minor aches and pains of muscles and joints associated with:

- simple backache
- arthritis
- strains
- bruises
- sprains

Warnings

For external use only. Avoid contact with the eyes and mucous membranes.

Ask a doctor before use if you have

allergic reactions to aspirin or salicylates.

When using this product

- use only as directed
- do not apply to wounds or damaged skin
- do not bandage tightly or use with a heating pad

Stop use and ask a doctor if

- condition worsens, or if symptoms persist for more than 7 days or clear up and occur again within a few days
- redness is present
- irritation of the skin develops

If pregnant or breast-feeding,

ask a health professional before use.

Keep out of reach of children.

If swallowed, get medical help or contact Poison Control Center right away

Directions

- Massage into affected area until thoroughly absorbed into the skin.
- Shake well before use.
- Fod individuals 12 years of age and older: Apply generously to the affected area not more than 4 times daily.
- Children under 12 years of age: Consult a doctor.

Inactive ingredients

Alcohol, DC Red#17, DC Yellow#11, Disodium EDTA, Eucalyptus Oil, Mineral Oil, Polysorbate 80, Purified Water